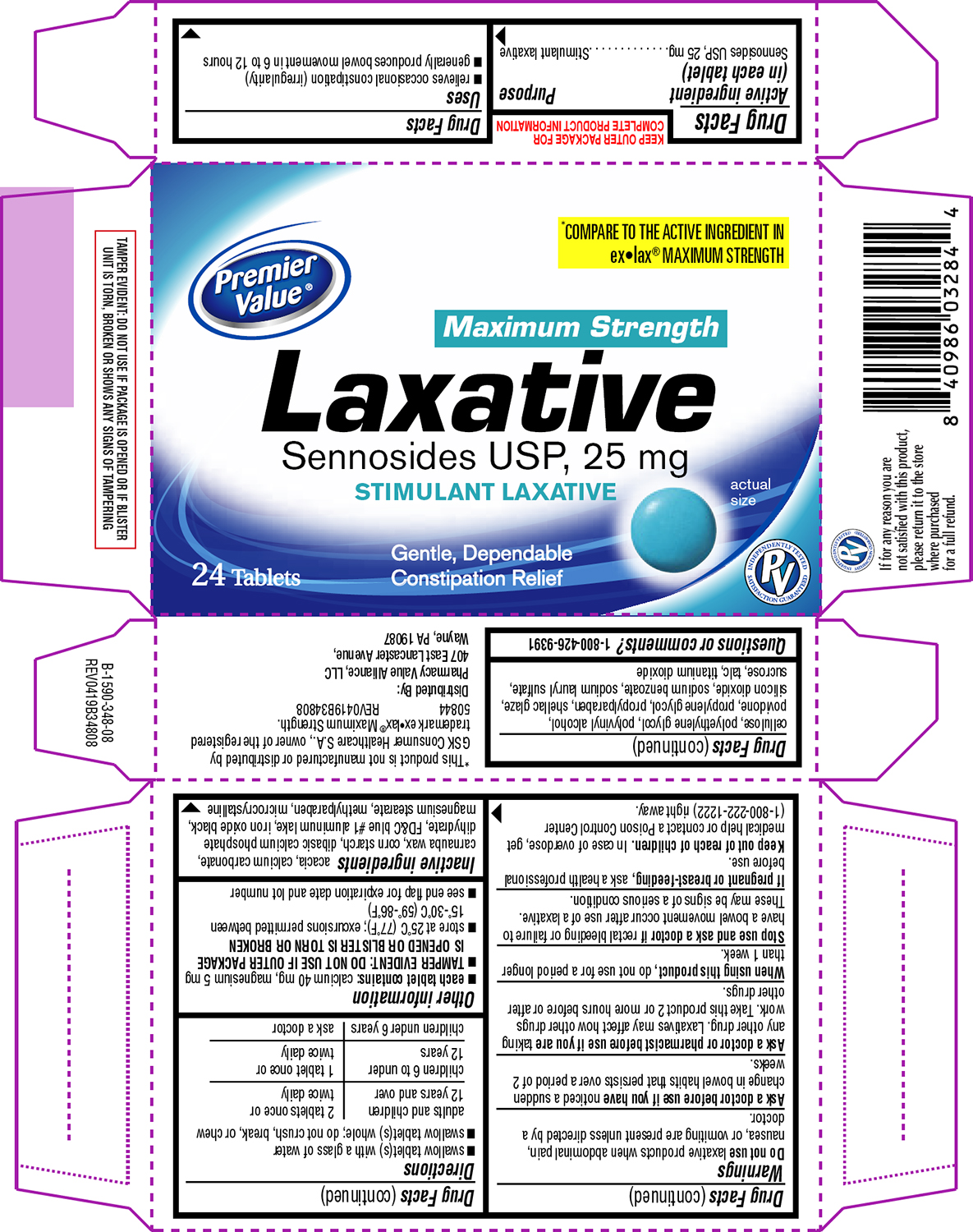 DRUG LABEL: Laxative
NDC: 68016-739 | Form: TABLET, SUGAR COATED
Manufacturer: Chain Drug Consortium
Category: otc | Type: HUMAN OTC DRUG LABEL
Date: 20250718

ACTIVE INGREDIENTS: SENNOSIDES 25 mg/1 1
INACTIVE INGREDIENTS: ACACIA; CALCIUM CARBONATE; CARNAUBA WAX; STARCH, CORN; DIBASIC CALCIUM PHOSPHATE DIHYDRATE; FD&C BLUE NO. 1 ALUMINUM LAKE; FERROSOFERRIC OXIDE; MAGNESIUM STEARATE; METHYLPARABEN; MICROCRYSTALLINE CELLULOSE; POLYETHYLENE GLYCOL, UNSPECIFIED; POLYVINYL ALCOHOL, UNSPECIFIED; POVIDONE, UNSPECIFIED; PROPYLENE GLYCOL; PROPYLPARABEN; SHELLAC; SILICON DIOXIDE; SODIUM BENZOATE; SODIUM LAURYL SULFATE; SUCROSE; TALC; TITANIUM DIOXIDE

Premier Value 44-348 Delisted

Active ingredient (in each tablet)

Sennosides USP, 25 mg

Purpose

Stimulant laxative

Uses

- relieves occasional constipation (irregularity)
- generally produces bowel movement in 6 to 12 hours

Warnings

Do not use

laxative products when abdominal pain, nausea, or vomiting are present unless directed by a doctor.

Ask a doctor before use if you have

noticed a sudden change in bowel habits that persists over a period of 2 weeks.

Ask a doctor or pharmacist before use if you are

taking any other drug. Laxatives may affect how other drugs work. Take this product 2 or more hours before or after other drugs.

When using this product,

do not use for a period longer than 1 week.

Stop use and ask a doctor if

rectal bleeding or failure to have a bowel movement occur after use of a laxative. These may be signs of a serious condition.

If pregnant or breast-feeding,

ask a health professional before use.

Keep out of reach of children.

In case of overdose, get medical help or contact a Poison Control Center (1-800-222-1222) right away.

Directions

- swallow tablet(s) with a glass of water
- swallow tablet(s) whole; do not crush, break, or chew

adults and children 12 years and over | 2 tablets once or twice daily
children 6 to under 12 years | 1 tablet once or twice daily
children under 6 years | ask a doctor

Other information

- each tablet contains: calcium 40 mg, magnesium 5 mg
- TAMPER EVIDENT: DO NOT USE IF OUTER PACKAGE IS OPENED OR BLISTER IS TORN OR BROKEN
- store at 25°C (77°F); excursions permitted between 15°-30°C (59°-86°F)
- see end flap for expiration date and lot number

Inactive ingredients

acacia, calcium carbonate, carnauba wax, corn starch, dibasic calcium phosphate dihydrate, FD&C blue #1 aluminum lake, iron oxide black, magnesium stearate, methylparaben, microcrystalline cellulose, polyethylene glycol, polyvinyl alcohol, povidone, propylene glycol, propylparaben, shellac glaze, silicon dioxide, sodium benzoate, sodium lauryl sulfate, sucrose, talc, titanium dioxide

Questions or comments?

1-800-426-9391

Principal Display Panel

Premier
Value®

*COMPARE TO THE ACTIVE INGREDIENT IN
ex•lax® MAXIMUM STRENGTH

Maximum Strength
Laxative
Sennosides USP, 25 mg
STIMULANT LAXATIVE

24 Tablets

actual
size

Gentle, Dependable
Constipation Relief

PV
INDEPENDENTLY TESTED
SATISFACTION GUARANTEED

TAMPER EVIDENT: DO NOT USE IF PACKAGE IS OPENED OR IF BLISTER
UNIT IS TORN, BROKEN OR SHOWS ANY SIGNS OF TAMPERING

*This product is not manufactured or distributed by
GSK Consumer Healthcare S.A., owner of the registered
trademark ex•lax® Maximum Strength.
50844 REV0419B34808

Distributed By:
Pharmacy Value Alliance, LLC
407 East Lancaster Avenue,
Wayne, PA 19087

If for any reason you are
not satisfied with this product,
please return it to the store
where purchased
for a full refund.

Premier Value 44-348